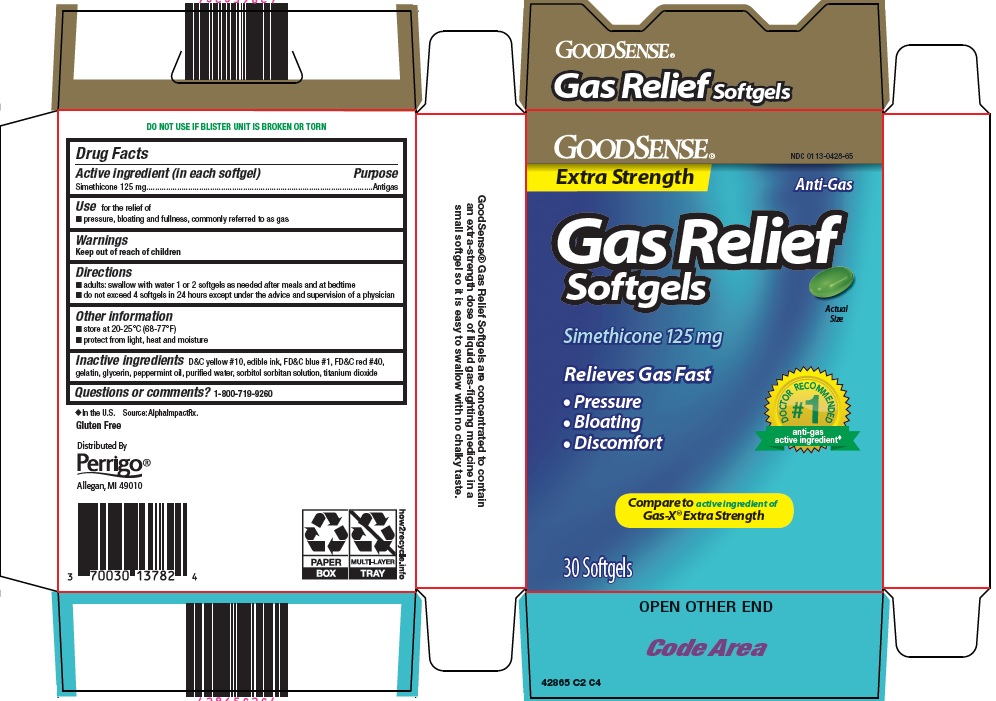 DRUG LABEL: Good Sense Gas Relief
NDC: 0113-0428 | Form: CAPSULE, LIQUID FILLED
Manufacturer: L. Perrigo Company
Category: otc | Type: HUMAN OTC DRUG LABEL
Date: 20241102

ACTIVE INGREDIENTS: DIMETHICONE 125 mg/1 1
INACTIVE INGREDIENTS: SILICON DIOXIDE; D&C YELLOW NO. 10; FD&C BLUE NO. 1; FD&C RED NO. 40; GELATIN, UNSPECIFIED; GLYCERIN; PEPPERMINT OIL; WATER; TITANIUM DIOXIDE

Perrigo Gas Relief Drug Facts

Active ingredient (in each softgel)

Simethicone 125 mg

Purpose

Antigas

Use

for the relief of

- pressure, bloating and fullness, commonly referred to as gas

Directions

- adults: swallow with water 1 or 2 softgels as needed after meals and at bedtime
- do not exceed 4 softgels in 24 hours except under the advice and supervision of a physician

Other information

- store at 20-25°C (68-77°F)
- protect from light, heat and moisture

Inactive ingredients

D&C yellow #10, edible ink, FD&C blue #1, FD&C red #40, gelatin, glycerin, peppermint oil, purified water, sorbitol sorbitan solution, titanium dioxide

Questions or comments?

1-800-719-9260

Principal Display Panel

Extra Strength

Anti-Gas

Gas Relief

Softgels

Actual Size

Simethicone 125 mg

Relieves Gas Fast

• Pressure

• Bloating

• Discomfort

#1 DOCTOR RECOMMENDED

anti-gas active ingredient

Compare to active ingredient of Gas-X® Extra Strength

30 Softgels